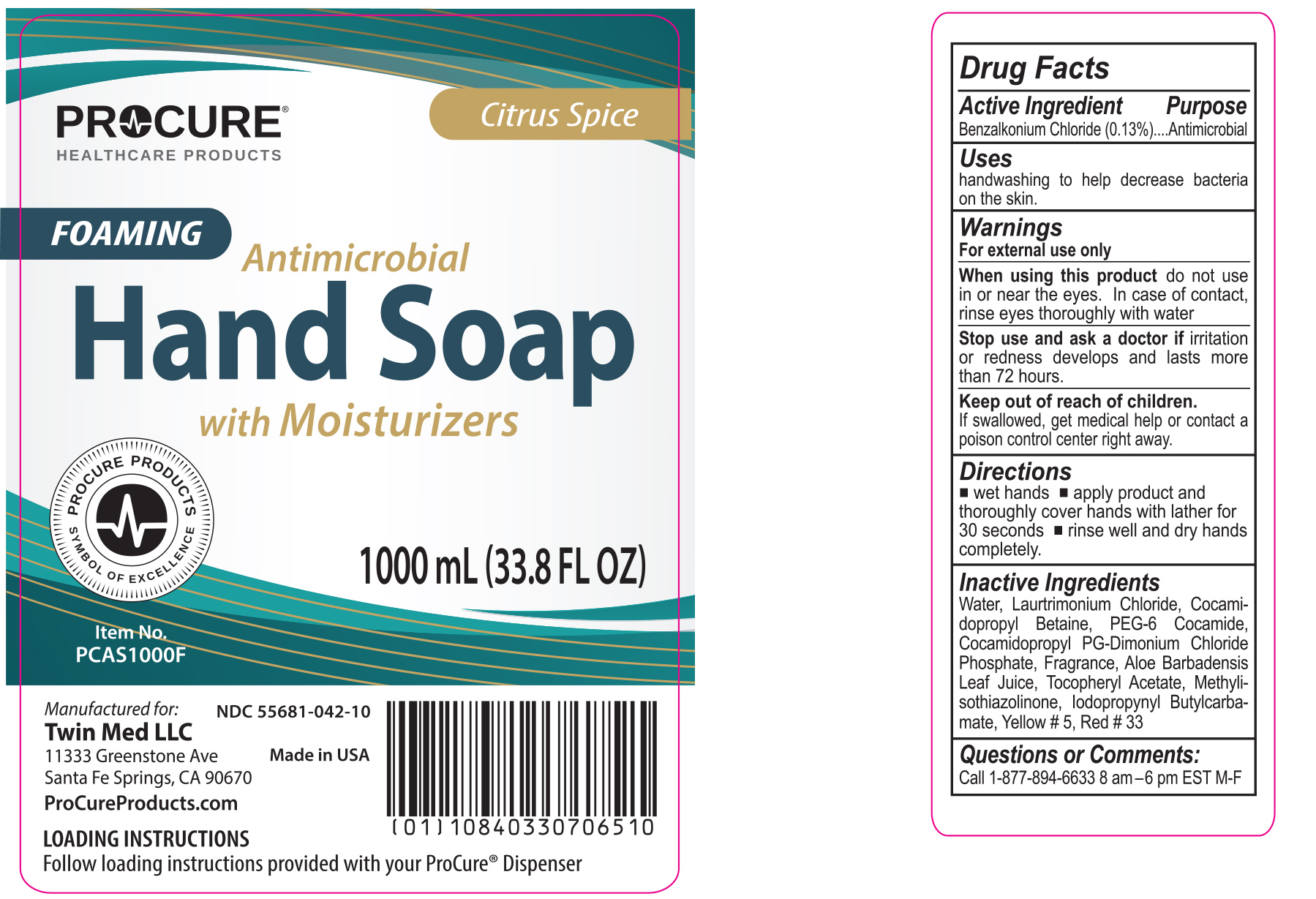 DRUG LABEL: ProCure Foaming Antimicrobial Hand
NDC: 55681-042 | Form: SOAP
Manufacturer: Twin Med LLC
Category: otc | Type: HUMAN OTC DRUG LABEL
Date: 20250904

ACTIVE INGREDIENTS: BENZALKONIUM CHLORIDE 0.13 g/100 mL
INACTIVE INGREDIENTS: PEG-6 COCAMIDE; METHYLISOTHIAZOLINONE; LAURTRIMONIUM CHLORIDE; ALOE VERA LEAF JUICE; COCAMIDOPROPYL BETAINE; WATER; IODOPROPYNYL BUTYLCARBAMATE; D&C RED NO. 33; COCAMIDOPROPYL PROPYLENE GLYCOL-DIMONIUM CHLORIDE PHOSPHATE; FD&C YELLOW NO. 5; .ALPHA.-TOCOPHEROL ACETATE

Active Ingredient

Benzalkonium Chloride 0.13%

Purpose

Antimicrobial

Uses

Uses handwashing to help decrease bacteria on the skin

Warnings

For external use only

When using this product do not use in or near the eyes. In case of contact, rinse eyes thoroughly with water

Stop use and ask a doctor if irritation or redness develops and lasts more than 72 hours

Keep out of reach of children. If swallowed, get medical help or contact a poison control center right away

Directions

- wet hands
- apply product and thoroughly cover hands with lather for 30 seconds
- rinse well and dry hands completely

Inactive Ingredients

Inactive Ingredients: Water, Laurtrimonium Chloride, Cocamidopropyl Betaine, PEG-6 Cocamide, Cocamidopropyl PG-Dimonium Chloride Phosphate, Fragrance, Aloe Barbadensis Leaf Juice, Tocopheryl Acetate, Methylisothiazolinone, Iodopropynyl Butylcarbamate, Yellow # 5, Red # 33